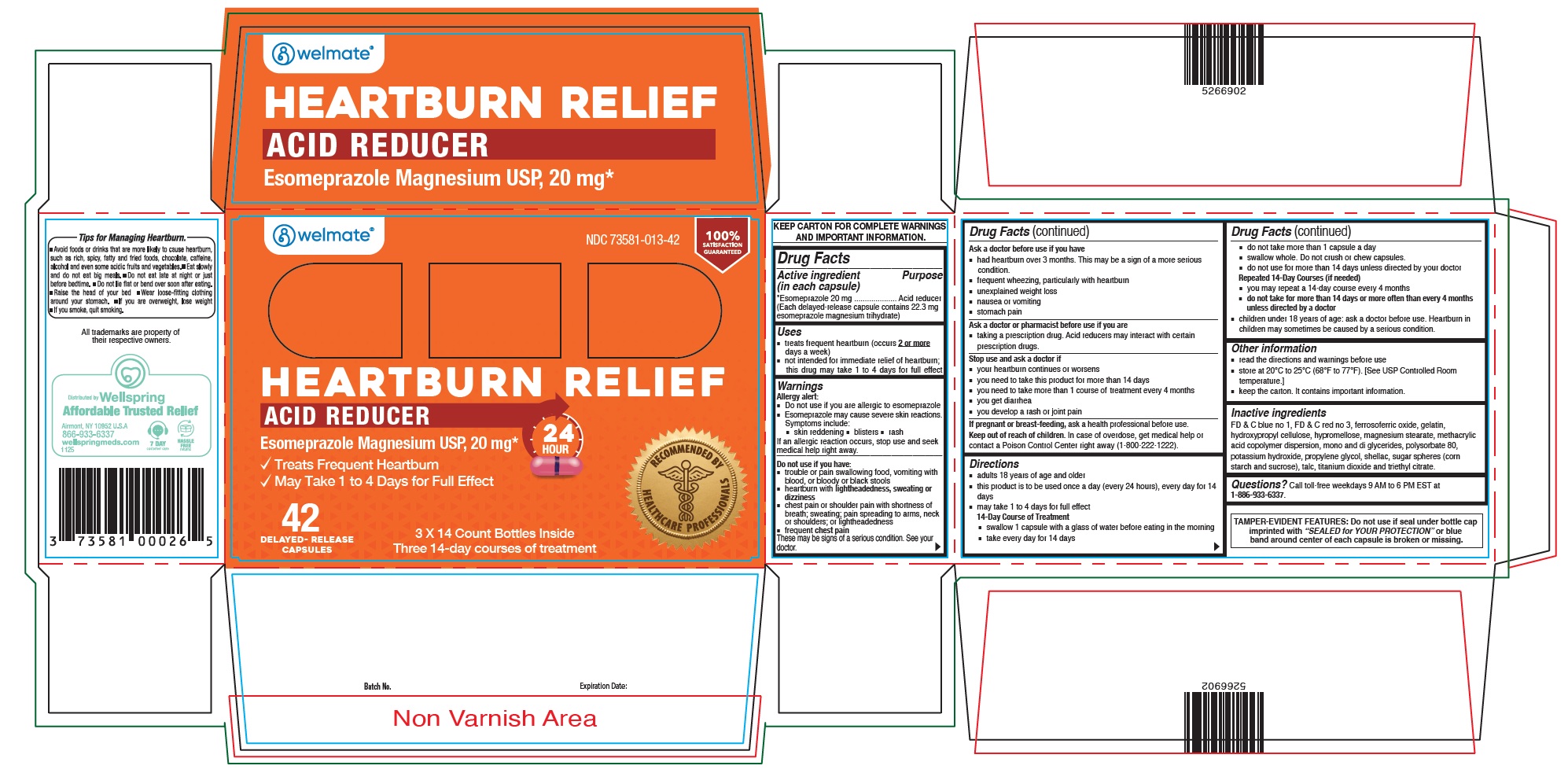 DRUG LABEL: Esomeprazole
NDC: 73581-013 | Form: CAPSULE, DELAYED RELEASE
Manufacturer: YYBA CORP
Category: otc | Type: HUMAN OTC DRUG LABEL
Date: 20251119

ACTIVE INGREDIENTS: ESOMEPRAZOLE MAGNESIUM 20 mg/1 1
INACTIVE INGREDIENTS: METHACRYLIC ACID AND ETHYL ACRYLATE COPOLYMER; POLYSORBATE 80; POTASSIUM HYDROXIDE; PROPYLENE GLYCOL; FERROSOFERRIC OXIDE; GELATIN, UNSPECIFIED; HYDROXYPROPYL CELLULOSE, UNSPECIFIED; HYPROMELLOSE 2208 (100 MPA.S); MAGNESIUM STEARATE; SHELLAC; TALC; TITANIUM DIOXIDE; TRIETHYL CITRATE; STARCH, CORN; SUCROSE; FD&C BLUE NO. 1; FD&C RED NO. 3; GLYCERYL MONOSTEARATE

Esomeprazole

Drug Facts

Active ingredient (in each capsule)

*Esomeprazole 20 mg (Each delayed-release capsule contains 22.3 mg esomeprazole magnesium trihydrate)

Purpose

Acid reducer

Use

- treats frequent heartburn (occurs 2 or moredays a week)
- not intended for immediate relief of heartburn; this drug may take 1 to 4 days for full effect

Warnings

Allergy alert:

- Do not use if you are allergic to esomeprazole
- Esomeprazole may cause severe skin reactions. Symptoms include:

- skin reddening

- blisters

- rash

- If an allergic reaction occurs, stop use and seek medical help right away.

Do not use if you have:

- trouble or pain swallowing food, vomiting with blood, or bloody or black stools
- heartburn with lightheadedness, sweating or dizziness
- chest pain or shoulder pain with shortness of breath; sweating; pain spreading to arms, neck or shoulders; or lightheadedness
- frequent chest pain

These may be signs of a serious condition. See your doctor.

Ask a doctor before use if you have:

- had heartburn over 3 months. This may be a sign of a more serious condition.
- frequent wheezing, particularly with heartburn
- unexplained weight loss
- nausea or vomiting
- stomach pain

Ask a doctor or pharmacist before use if you are

- taking a prescription drug. Acid reducers may interact with certain prescription drugs.

Stop use and ask a doctor if

- your heartburn continues or worsens
- you need to take this product for more than 14 days
- you need to take more than 1 course of treatment every 4 months
- you get diarrhea
- you develop a rash or joint pain

If pregnant or breast-feeding,

ask a health professional before use.

Keep out of reach of children.

In case of overdose, get medical help or contact a Poison Control Center right away (1-800-222-1222).

Directions

- adults 18 years of age and older
- this product is to be used once a day (every 24 hours), every day for 14 days
- may take 1 to 4 days for full effect
  14-Day Course of Treatment
- swallow 1 capsule with a glass of water before eating in the morning
- take every day for 14 days
- do not take more than 1 capsule a day
- swallow whole. Do not crush or chew capsules.
- do not use for more than 14 days unless directed by your doctor
- Repeated 14-Day Courses (if needed)
- you may repeat a 14-day course every 4 months
- do not take for more than 14 days or more often than every 4 months unless directed by a doctor
- children under 18 years of age: ask a doctor before use. Heartburn in children may sometimes be caused by a serious condition.

Other information

- read the directions and warnings before use.
- Store at 20°C to 25°C (68°F to 77°F). [See USP controlled room temperature.]
- keep the carton. It contains important information.

Inactive Ingredients

FD & C blue no 1, FD & C red no 3, ferrosoferric oxide, gelatin, hydroxypropyl cellulose, hypromellose, magnesium stearate, methacrylic acid copolymer dispersion, mono and di glycerides, polysorbate 80, potassium hydroxide, propylene glycol, shellac, sugar spheres (corn starch and sucrose), talc, titanium dioxide and triethyl citrate.

Questions?

Call toll-free weekdays 9 AM to 6 PM EST at 866-933-6337.

TAMPER-EVIDENT FEATURES: Do not use if seal under bottle cap imprinted with "SEALED for YOUR PROTECTION"or blue band around center of each capsule is broken or missing.

Tips for Managing Heartburn

- Avoid foods or drinks that are more likely to cause heartburn, such as rich, spicy, fatty and fried foods, chocolate, caffeine, alcohol and even some acidic fruits and vegetables.
- Eat slowly and do not eat big meals.
- Do not eat late at night or just before bedtime.
- Do not lie flat or bend over soon after eating.
- Raise the head of your bed.
- Wear loose-fitting clothing around your stomach.
- If you are overweight, lose weight.
- If you smoke, quit smoking.

Distributed by:
Wellspring
Airmont, NY 10952, U.S.A.

R0922

PRINCIPAL DISPLAY PANEL - 42 Capsule Bottle Carton

welmate®

NDC 73581-013-42

HEARTBURN RELIEF
ACID REDUCER
Esomeprazole Magnesium USP, 20 mg*

✓Treats Frequent Heartburn

✓May Take 1 to 4 Days for Full Effect

24

HOUR

42 DELAYED-RELEASE CAPSULES

3 X 14 Count Bottles Inside
Three 14-day courses of treatment

RECOMMENDED BY HEALTHCARE PROFESSIONALS